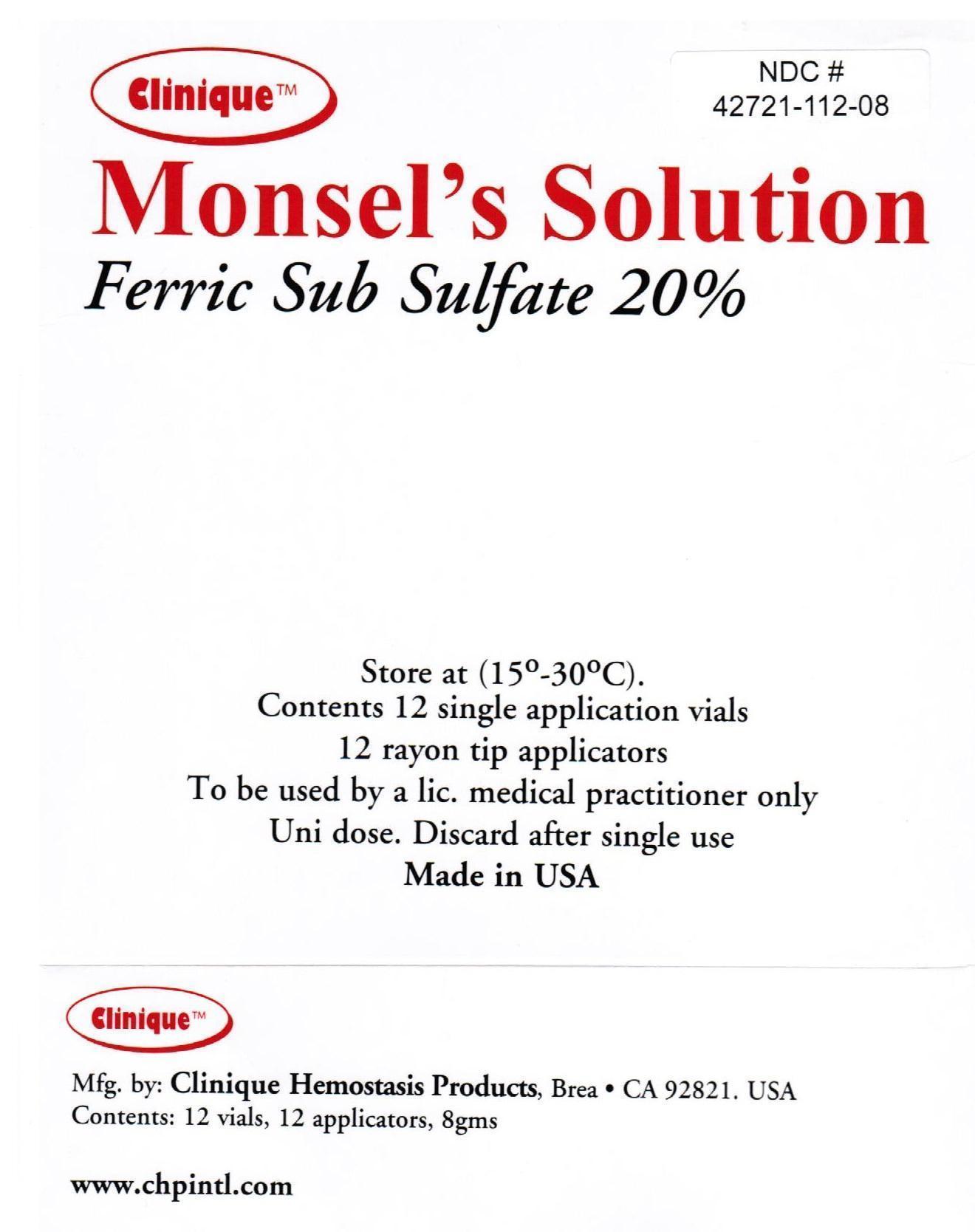 DRUG LABEL: Monsels solution
NDC: 42721-112 | Form: LIQUID
Manufacturer: BIODIAGNOSTIC INTERNATIONAL
Category: prescription | Type: HUMAN PRESCRIPTION DRUG LABEL
Date: 20180301

ACTIVE INGREDIENTS: FERRIC SUBSULFATE 20 g/100 g
INACTIVE INGREDIENTS: WATER

Monsel's solution

DESCRIPTION

Ferric Sub sulfate 20%

STORAGE AND HANDLING

Store at (15-30C)

HOW SUPPLIED

Contents 12 single application vials
12 rayon tip applicators

INDICATIONS AND USAGE

Used as a styptic in its undiluted form.

PRECAUTIONS

To be used by a lic. Medical practitioner only.

Uni dose. Discard after single use.